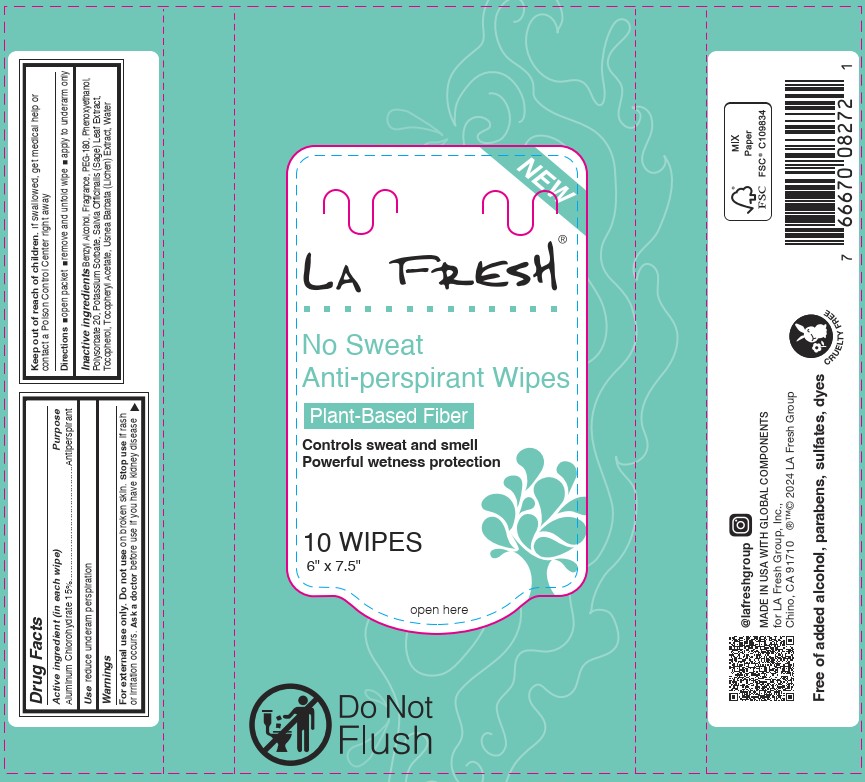 DRUG LABEL: LA FRESH Antiperspirant Wipe
NDC: 64709-161 | Form: CLOTH
Manufacturer: Diamond Wipes International, Inc
Category: otc | Type: HUMAN OTC DRUG LABEL
Date: 20251124

ACTIVE INGREDIENTS: ALUMINUM CHLOROHYDRATE 0.15 g/1 g
INACTIVE INGREDIENTS: SAGE; USNEA BARBATA; TOCOPHEROL; WATER; BENZYL ALCOHOL; PHENOXYETHANOL; POTASSIUM SORBATE; POLYSORBATE 20; PEG-180; .ALPHA.-TOCOPHEROL ACETATE

LA FRESH Antiperspirant Wipe

Active ingredient

Aluminum Chlorohydrate 15%

Purpose

Antiperspirant

Use

reduce underarm perspiration

Warnings

For external use only. Do not use on broken skin. Stop use if rash or irritation occurs. Ask a doctor before use if you have kidney disease

Keep out of reach of children. If swallowed, get medical help or contact a Poison Control Center right away

Directions

■open packet ■remove and unfold wipe ■apply to underarm only

Inactive ingredients

Benzoic Acid, Benzyl Alcohol, Chlorphenesin, Fragrance, PEG-180, Phenoxyethanol, Polysorbate 20, Potassium Sorbate, Salvia Officinalis (Sage) Leaf Extract, Sorbic Acid, Tocopherol, Tocopheryl Acetate, Usnea Barbata (Lichen) Extract, Water

Label

LA Fresh®

No Sweat

Anti-perspirant Wipes

Plant- Based Fiber

Controls sweat and smell

Powerful wetness protection

10 WIPES

6' x 7.5'

open here

Do Not Flush